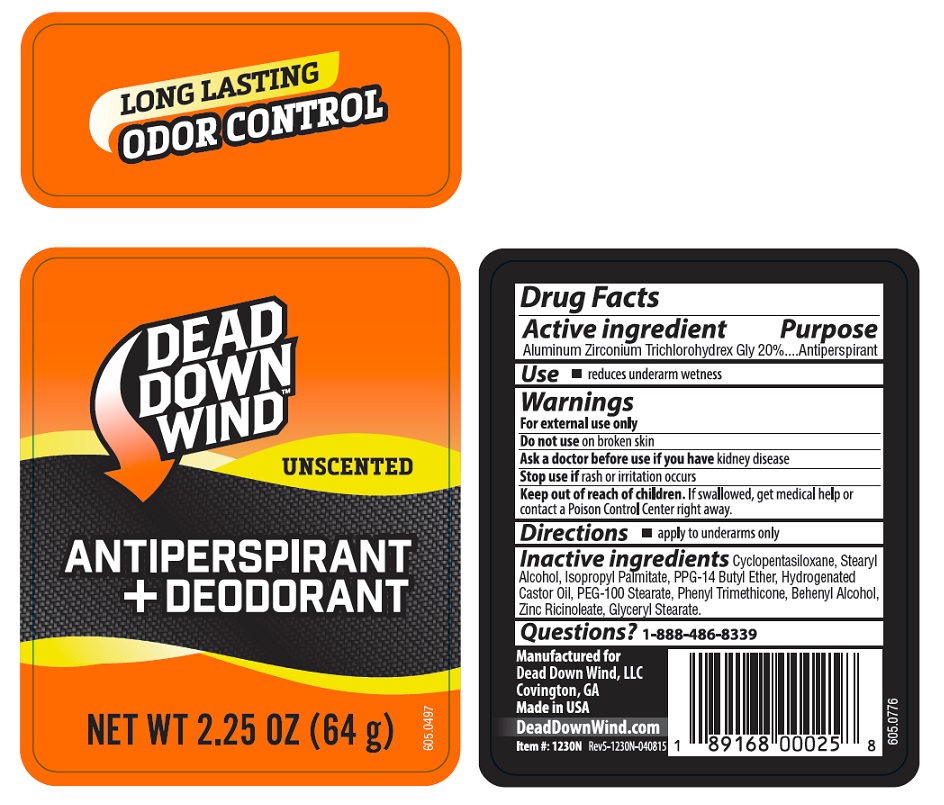 DRUG LABEL: Dead Down Wind Antiperspirant
NDC: 10889-426 | Form: STICK
Manufacturer: VVF Kansas Services LLC
Category: otc | Type: HUMAN OTC DRUG LABEL
Date: 20221229

ACTIVE INGREDIENTS: ALUMINUM ZIRCONIUM TRICHLOROHYDREX GLY 20 g/100 g
INACTIVE INGREDIENTS: CYCLOMETHICONE 5; PEG-100 STEARATE; PHENYL TRIMETHICONE; STEARYL ALCOHOL; ISOPROPYL PALMITATE; HYDROGENATED CASTOR OIL; GLYCERYL STEARATE SE; PPG-14 BUTYL ETHER; DOCOSANOL; ZINC RICINOLEATE

Dead Down Wind Scent Prevent® Antiperspirant

Active ingredient

Aluminum Zirconium Trichlorohydrex Gly 20%

Purpose

Antiperspirant

Use

- reduces underarm dampness

Warnings

For external use only

Do not use on broken skin

Ask doctor before use if you have kidney disease

Stop use if rash or irritation occurs

Keep out of reach of children.

If swallowed, get medical help or contact a Poison Control Center right away.

Directions

- Apply to underarms only

Inactive ingredients

Cyclopentasiloxane, Stearyl Alcohol, Isopropyl Palmitate,

PPG-14 Butyl Ether, Hydrogenated Castor Oil, PEG-100 Stearate,

Phenyl Trimethicone, Behenyl Alcohol, Zinc Ricinoleate,

Glyceryl Stearate.

Questions?

1-888-486-8339

Manufactured for
Dead Down Wind LLC
Covington, GA
Made in USA
DeadDownWind.com

UPC: 1 89168 00025 8

LONG LASTING

ODOR CONTROL

DEAD DOWN WIND™

UNSCENTED

ANTIPERSPIRANT + DEODORANT

NET WT 2.25 OZ (64 g)